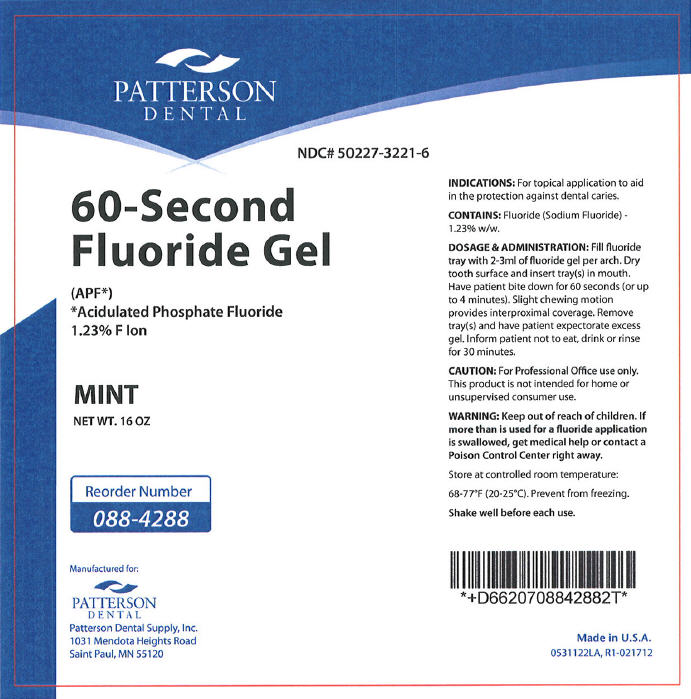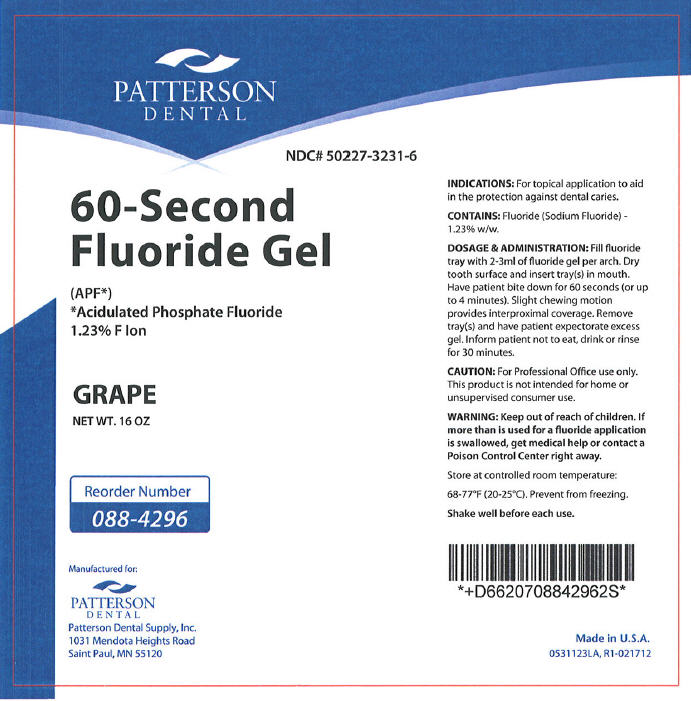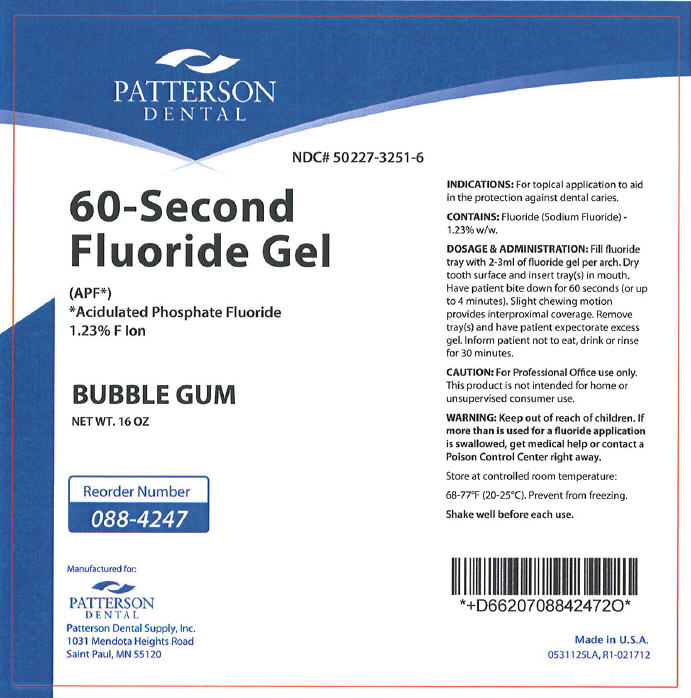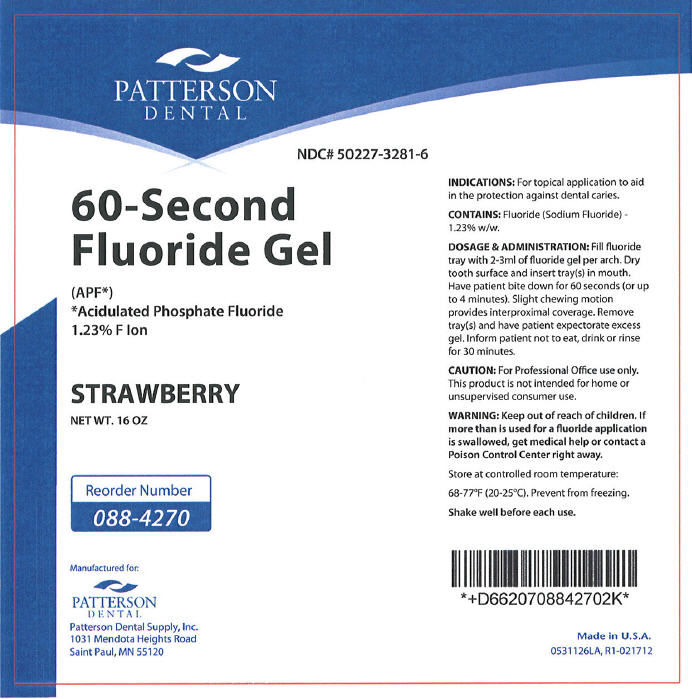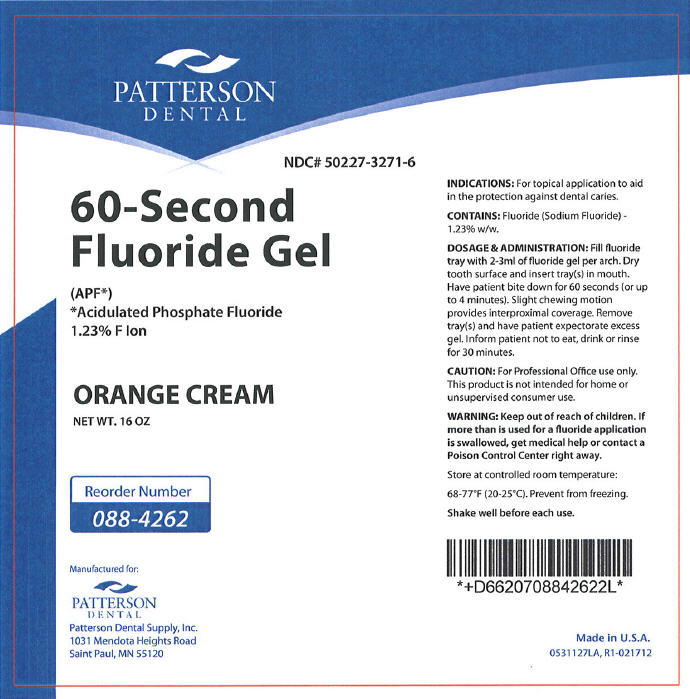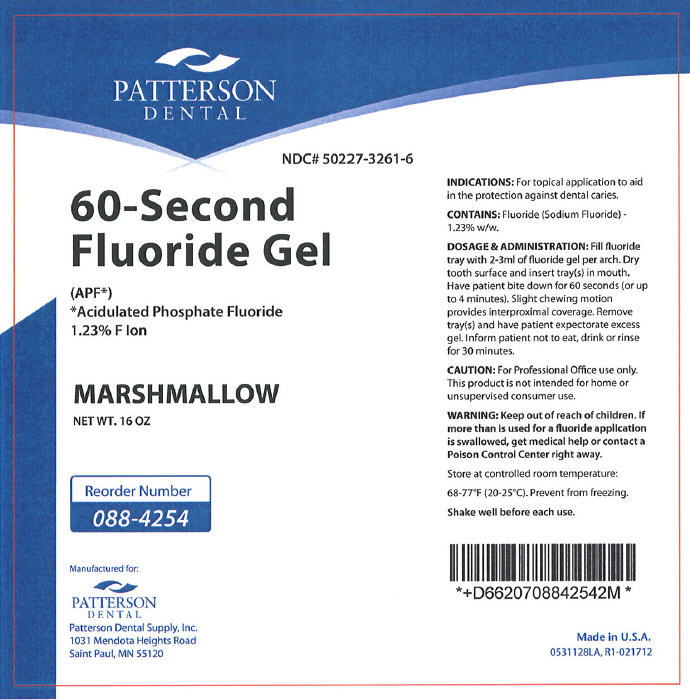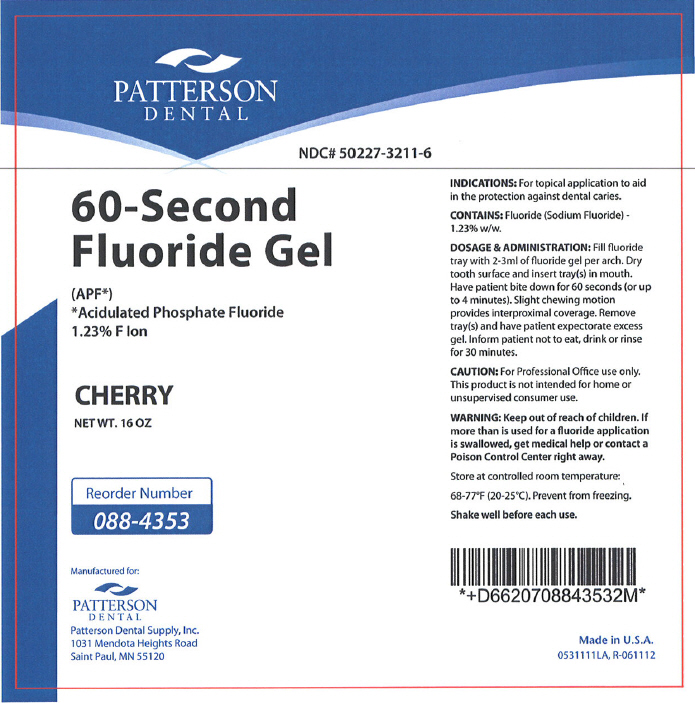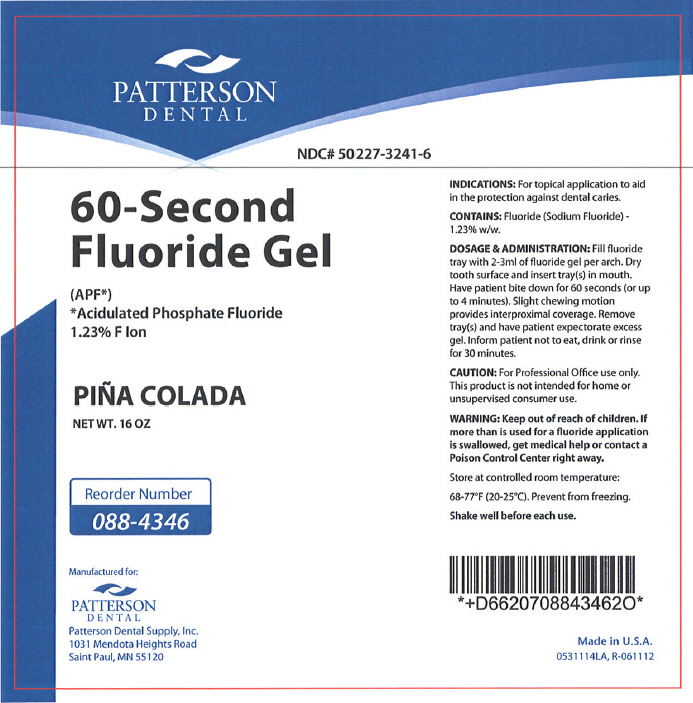 DRUG LABEL: 60-Second Fluoride 
NDC: 50227-3221 | Form: GEL
Manufacturer: Patterson Dental Supply Inc
Category: prescription | Type: HUMAN PRESCRIPTION DRUG LABEL
Date: 20121009

ACTIVE INGREDIENTS: Sodium Fluoride 12.3 mg/1 g
INACTIVE INGREDIENTS: Water; MAGNESIUM ALUMINUM SILICATE; Phosphoric Acid; Hydrofluoric Acid; Anhydrous Citric Acid; Xanthan Gum; Xylitol; Polysorbate 20; SACCHARIN SODIUM DIHYDRATE; Sodium Benzoate; Titanium Dioxide

60-Second Fluoride Gel

INDICATIONS

For topical application to aid in the protection against dental caries.

CONTAINS

Fluoride (Sodium Fluoride) – 1.23% w/w.

DOSAGE & ADMINISTRATION

Fill fluoride tray with 2-3ml of fluoride gel per arch. Dry tooth surface and insert tray(s) in mouth. Have patient bite down for 60 seconds (or up to 4 minutes). Slight chewing motion provides interproximal coverage. Remove tray(s) and have patient expectorate excess gel. Inform patient not to eat, drink or rinse for 30 minutes.

CAUTION

For Professional Office use only. This product is not intended for home or unsupervised consumer use.

WARNING

Keep out of reach of children. If more than is used for a fluoride application is swallowed, get medical help or contact a Poison Control Center right away.

HOW SUPPLIED

STORAGE AND HANDLING

Store at controlled room temperature:

68-77°F (20-25°C). Prevent from freezing.

Shake well before each use.

Made in U.S.A.

PRINCIPAL DISPLAY PANEL - 454 g Mint Bottle Label

PATTERSON
DENTAL

NDC# 50227-3221-6

60-Second
Fluoride Gel

(APF*)
*Acidulated Phosphate Fluoride
1.23% F Ion

MINT

NET WT. 16 OZ

Reorder Number
088-4288

Manufactured for:
PATTERSON
DENTAL
Patterson Dental Supply, Inc.
1031 Mendota Heights Road
Saint Paul, MN 55120

PRINCIPAL DISPLAY PANEL - 454 g Grape Bottle Label

PATTERSON
DENTAL

NDC# 50227-3231-6

60-Second
Fluoride Gel

(APF*)
*Acidulated Phosphate Fluoride
1.23% F Ion

GRAPE

NET WT. 16 OZ

Reorder Number
088-4296

Manufactured for:
PATTERSON
DENTAL
Patterson Dental Supply, Inc.
1031 Mendota Heights Road
Saint Paul, MN 55120

PRINCIPAL DISPLAY PANEL - 454 g Bubble Gum Bottle Label

PATTERSON
DENTAL

NDC# 50227-3251-6

60-Second
Fluoride Gel

(APF*)
*Acidulated Phosphate Fluoride
1.23% F Ion

BUBBLE GUM

NET WT. 16 OZ

Reorder Number
088-4247

Manufactured for:
PATTERSON
DENTAL
Patterson Dental Supply, Inc.
1031 Mendota Heights Road
Saint Paul, MN 55120

PRINCIPAL DISPLAY PANEL - 454 g Strawberry Bottle Label

PATTERSON
DENTAL

NDC# 50227-3281-6

60-Second
Fluoride Gel

(APF*)
*Acidulated Phosphate Fluoride
1.23% F Ion

STRAWBERRY

NET WT. 16 OZ

Reorder Number
088-4270

Manufactured for:
PATTERSON
DENTAL
Patterson Dental Supply, Inc.
1031 Mendota Heights Road
Saint Paul, MN 55120

PRINCIPAL DISPLAY PANEL - 454 g Orange Cream Bottle Label

PATTERSON
DENTAL

NDC# 50227-3271-6

60-Second
Fluoride Gel

(APF*)
*Acidulated Phosphate Fluoride
1.23% F Ion

ORANGE CREAM

NET WT. 16 OZ

Reorder Number
088-4262

Manufactured for:
PATTERSON
DENTAL
Patterson Dental Supply, Inc.
1031 Mendota Heights Road
Saint Paul, MN 55120

PRINCIPAL DISPLAY PANEL - 454 g Marshmallow Bottle Label

PATTERSON
DENTAL

NDC# 50227-3261-6

60-Second
Fluoride Gel

(APF*)
*Acidulated Phosphate Fluoride
1.23% F Ion

MARSHMALLOW

NET WT. 16 OZ

Reorder Number
088-4254

Manufactured for:
PATTERSON
DENTAL
Patterson Dental Supply, Inc.
1031 Mendota Heights Road
Saint Paul, MN 55120

PRINCIPAL DISPLAY PANEL - 454 g Cherry Bottle Label

PATTERSON
DENTAL

NDC# 50227-3211-6

60-Second
Fluoride Gel

(APF*)
*Acidulated Phosphate Fluoride
1.23% F Ion

CHERRY

NET WT. 16 OZ

Reorder Number
088-4353

Manufactured for:
PATTERSON
DENTAL
Patterson Dental Supply, Inc.
1031 Mendota Heights Road
Saint Paul, MN 55120

PRINCIPAL DISPLAY PANEL - 454 g Piña Colada Bottle Label

PATTERSON
DENTAL

NDC# 50227-3241-6

60-Second
Fluoride Gel

(APF*)
*Acidulated Phosphate Fluoride
1.23% F Ion

PIÑA COLADA

NET WT. 16 OZ

Reorder Number
088-4346

Manufactured for:
PATTERSON
DENTAL
Patterson Dental Supply, Inc.
1031 Mendota Heights Road
Saint Paul, MN 55120